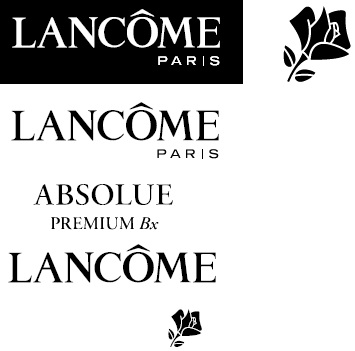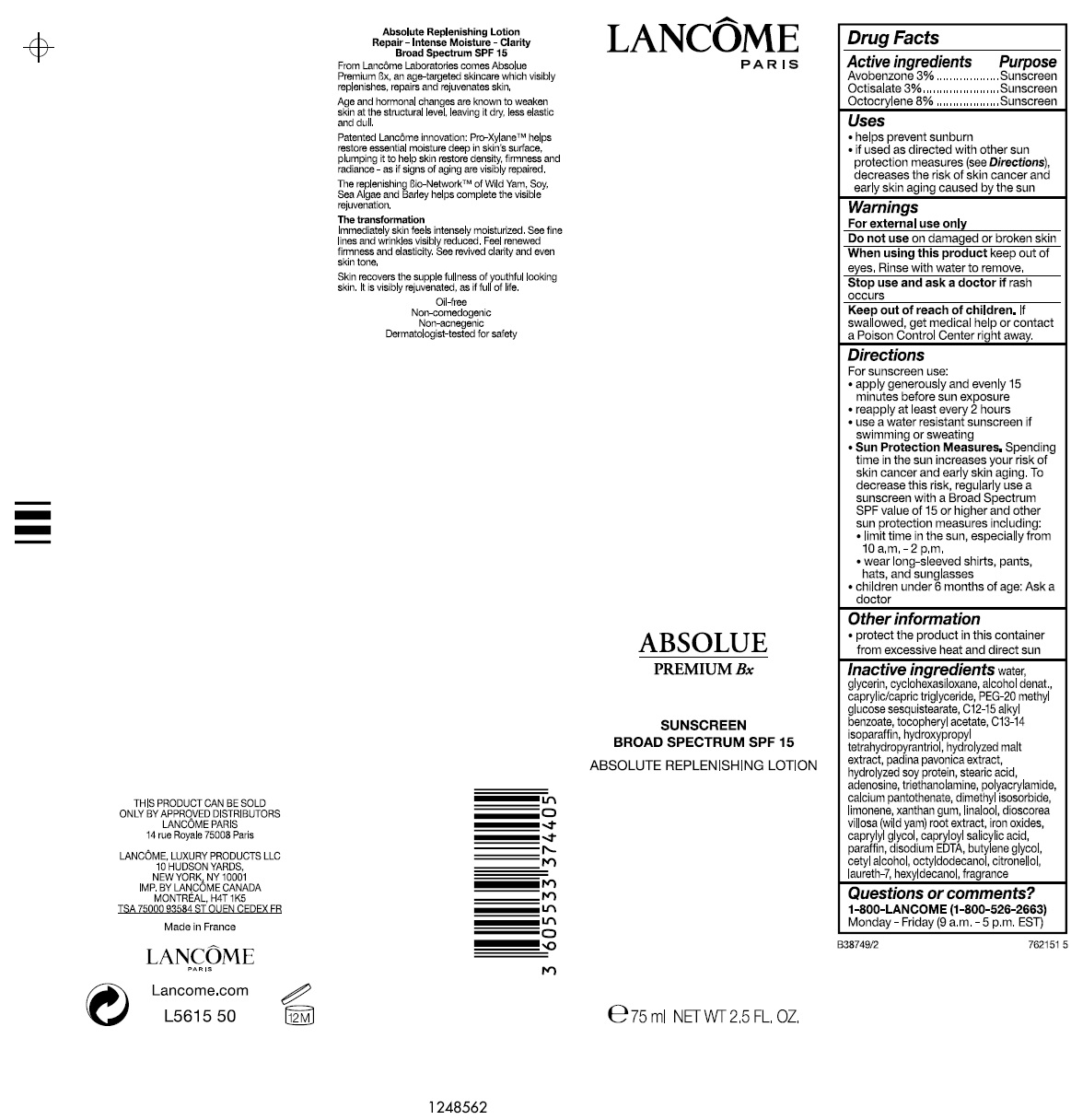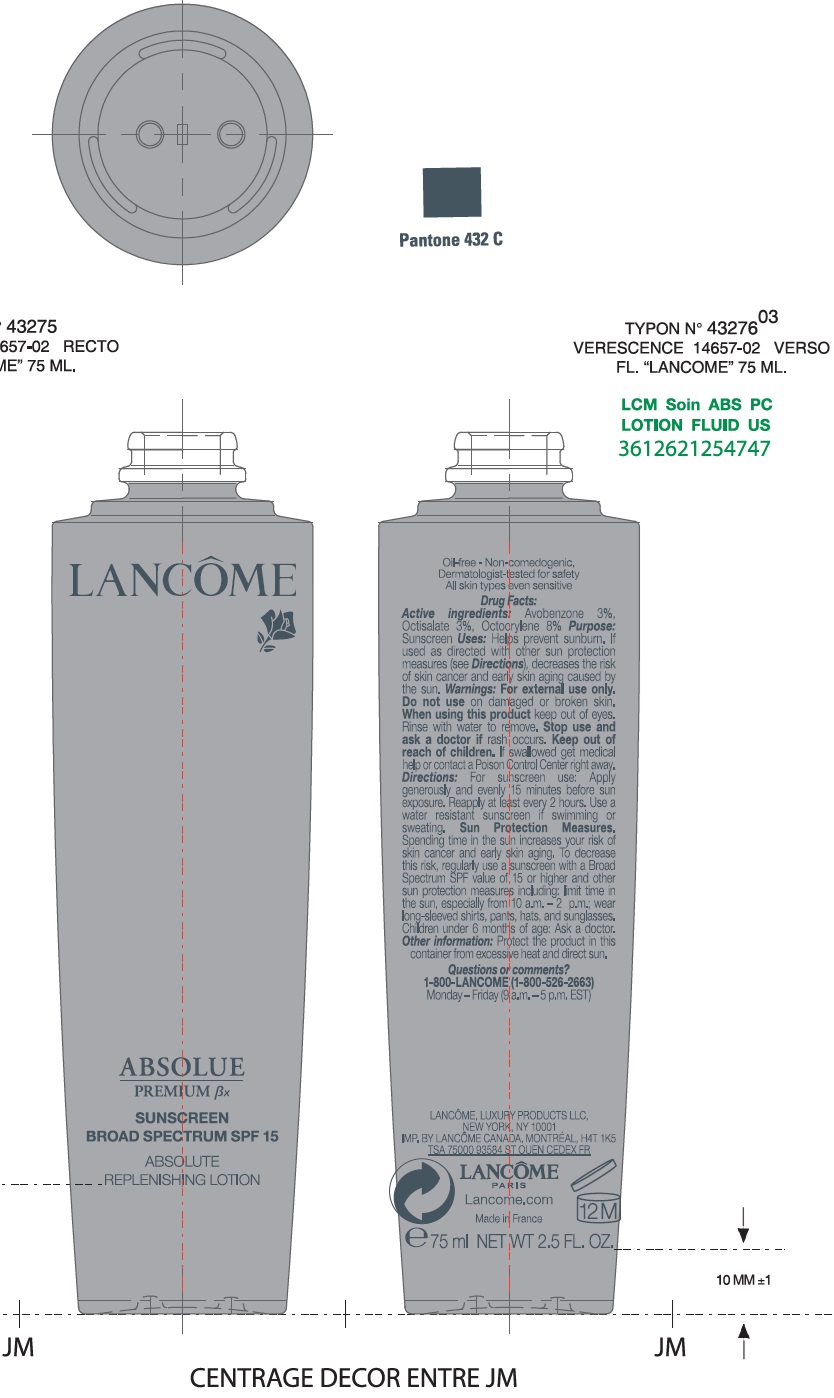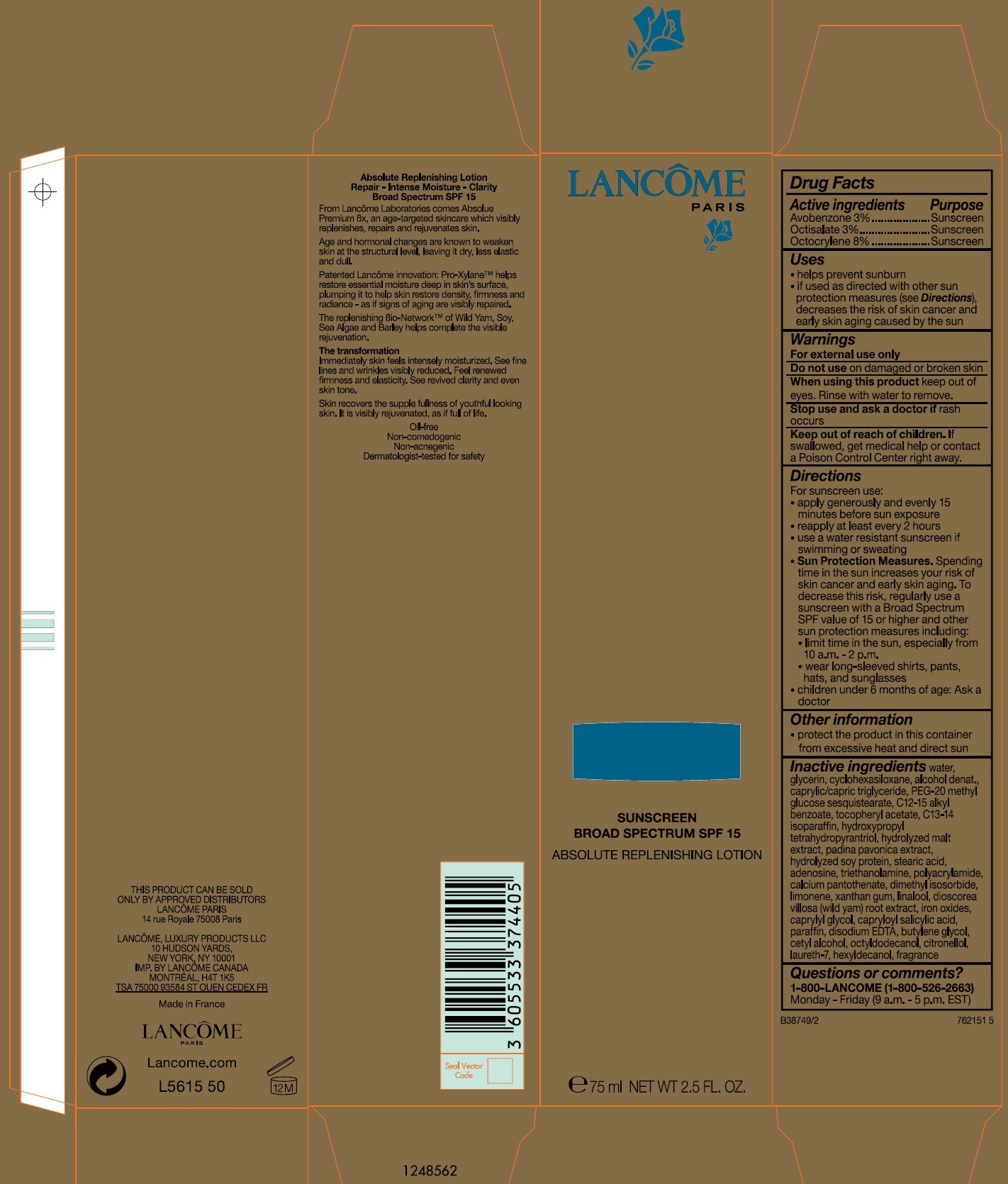 DRUG LABEL: Absolue Premium Bx Sunscreen Broad Spectrum SPF 15 Absolute Replenishing
NDC: 70581-003 | Form: CREAM
Manufacturer: BPS 60
Category: otc | Type: HUMAN OTC DRUG LABEL
Date: 20241121

ACTIVE INGREDIENTS: AVOBENZONE 30 mg/1 mL; OCTISALATE 30 mg/1 mL; OCTOCRYLENE 80 mg/1 mL
INACTIVE INGREDIENTS: WATER; GLYCERIN; CYCLOMETHICONE 6; ALCOHOL; MEDIUM-CHAIN TRIGLYCERIDES; PEG-20 METHYL GLUCOSE SESQUISTEARATE; ALKYL (C12-15) BENZOATE; .ALPHA.-TOCOPHEROL ACETATE; C13-14 ISOPARAFFIN; HYDROXYPROPYL TETRAHYDROPYRANTRIOL; PADINA PAVONICA; HYDROLYZED SOY PROTEIN (ENZYMATIC; 2000 MW); STEARIC ACID; ADENOSINE; TROLAMINE; CALCIUM PANTOTHENATE; DIMETHYL ISOSORBIDE; XANTHAN GUM; LINALOOL, (+/-)-; DIOSCOREA VILLOSA TUBER; FERRIC OXIDE RED; CAPRYLYL GLYCOL; CAPRYLOYL SALICYLIC ACID; PARAFFIN; EDETATE DISODIUM; BUTYLENE GLYCOL; CETYL ALCOHOL; OCTYLDODECANOL; LAURETH-7; HEXYLDECANOL

Absolue Premium Bx Sunscreen Broad Spectrum SPF 15 Absolute Replenishing Lotion

Active ingredients

Avobenzone 3%

Octisalate 3%

Octocrylene 8%

Purpose

Sunscreen

Uses

- helps prevent sunburn
- if used as directed with other sun protection measures (see Directions), decreases the risk of skin cancer and early skin aging caused by the sun

Warnings

For external use only

Do not use

on damaged or broken skin

When using this product

keep out of eyes, Rinse with water to remove.

Stop use and ask a doctor

if rash occurs

Keep out of reach of children.

If swallowed, get medical help or contact a Poison Control Center right away.

Directions

For sunscreen use:

- apply generously and evenly 15 minutes before sun exposure
- reapply at least every 2 hours
- use a water resistant sunscreen if swimming or sweating
- Sun Protection Measures.Spending time in the sun increases your risk of skin cancer and early skin aging. To decrease this risk. regularly use a sunscreen with a Broad Spectrum SPF value of 15 or higher and other sun protection measures including:
- limit time in the sun. especially from 10 a.m. - 2 p.m.
- wear long-sleeved shirts, pants, hats and sunglasses
- children under 6 months of age: Ask a doctor

Other information

- protect the product in this container from excessive heat and direct sun

Inactive ingredients

water, glycerin, cyclohexasiloxane, alcohol denat., caprylic/capric triglyceride, PEG-20 methyl glucose sesquistearate, C12-15 alkyl benzoate, tocopheryl acetate, C13-14 isoparaffin, hydroxypropyl tetrahydropyrantriol, hydrolyzed malt extract, padina pavonica extract, hydrolyzed soy protein, stearic acid, adenosine, triethanolamine, polyacrylamide, calcium pantothenate, dimethyl isosorbide, limonene, xanthan gum, linalool, dioscorea villosa (wild yam) root extract, iron oxides, caprylyl glycol, capryloyl salicylic acid, paraffin, disodium EDTA, butylene glycol, cetyl alcohol, octyldodecanol, citronellol, laureth-7, hexyldecanol, fragrance

Questions or comments?

1-800-LANCOME (1-800-526-2663)Monday - Friday (9 a.m. - 5 p.m. EST)